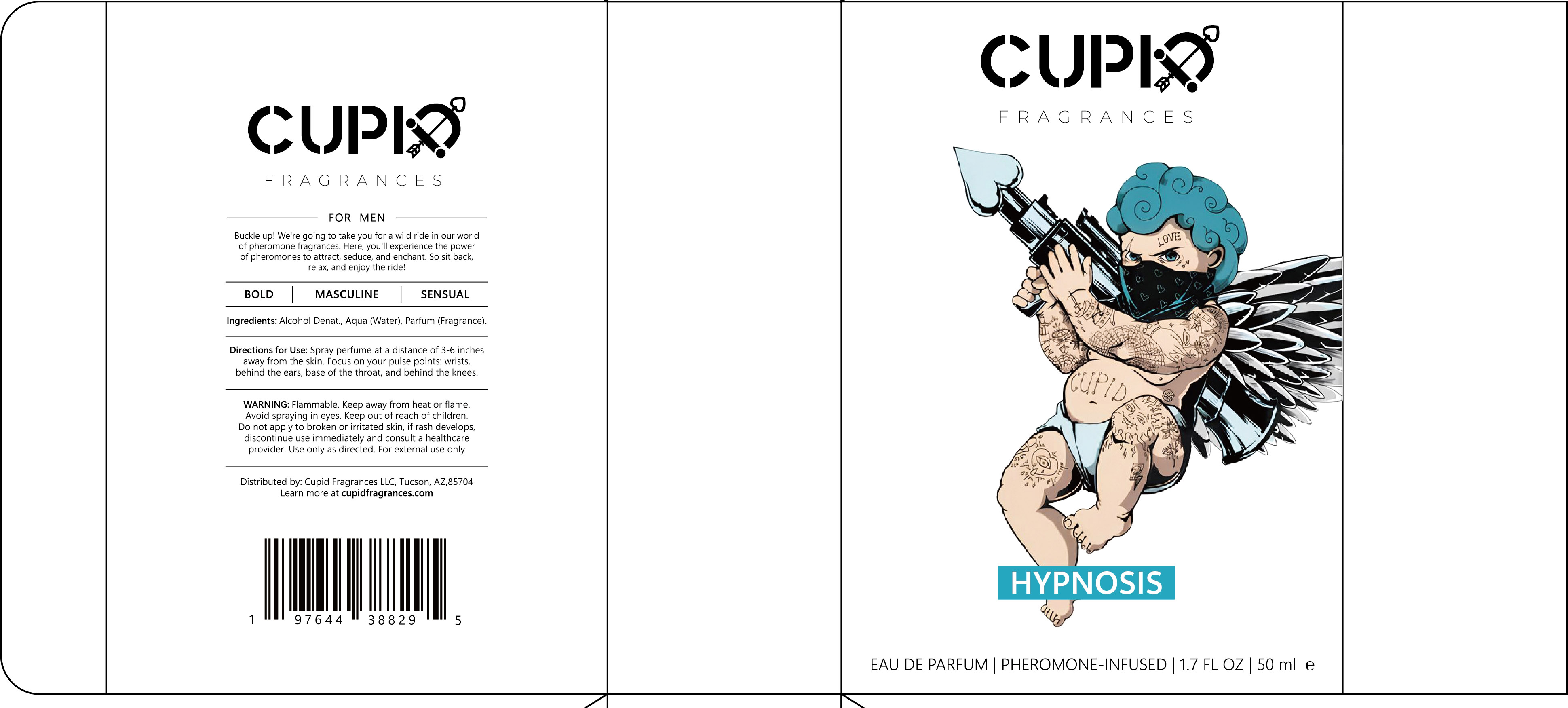 DRUG LABEL: perfume
NDC: 84732-058 | Form: LIQUID
Manufacturer: Dongguan Haiyi Technology Co.,Ltd.
Category: otc | Type: HUMAN OTC DRUG LABEL
Date: 20241021

ACTIVE INGREDIENTS: WATER 1 mg/50 mL
INACTIVE INGREDIENTS: ALCOHOL; PARFUMIDINE

Active ingredient

Aqua (Water)

Inactive ingredient

Alcohol Denat., Parfum (Fragrance).

Purpose section

Buckle up! We're going to take you for a wild ride in our worldof pheromone fragrances. Here, you'll experience the powerof pheromones to attract, seduce, and enchant. So sit back,relax, and enjoy the ride!

Warning

1).For external use only, avoid directcontact with eyes, lf you feel any
discomfort, stop using itand wash it with plenty of water. In severe cases,
pleaseseek medical attention in time.
2). Not allowed to be used ondamaged skin,

stop use

This product may cause allergic reactions in asmall number of people.
lf youexperience any discomfort,please stop using it immediately.

not use

Not suitable for use by children, pregnantor breast feeding people.

OUT OF CHILDREN

KEEP THE PRODUCT OUT OF REACH OF CHILDREN to

HOW TO USE

Spray perfume at a distance of 3-6 inchesaway from the skin. Focus on your pulse points: wrists,behind the ears, base of the throat, and behind the knees.

Dosage

take an appropriateamount,Use 2-3 times a week